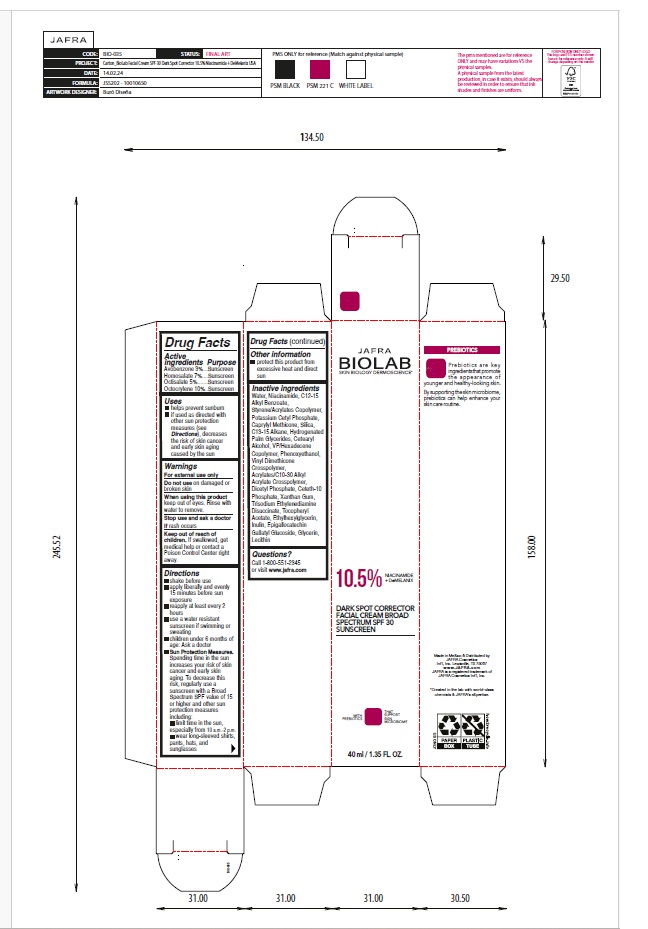 DRUG LABEL: JAFRA BIOLAB DARK SPOT CORRECTOR FACIAL cream BROAD SPECTRUM SPF 30 SUNSCREEN
NDC: 68828-602 | Form: CREAM
Manufacturer: Distribuidora Comercial Jafra, S.A. de C.V.
Category: otc | Type: HUMAN OTC DRUG LABEL
Date: 20250520

ACTIVE INGREDIENTS: AVOBENZONE 3 g/100 mL; HOMOSALATE 7 g/100 mL; OCTISALATE 5 g/100 mL; OCTOCRYLENE 10 g/100 mL
INACTIVE INGREDIENTS: ETHYLHEXYLGLYCERIN; GLYCERIN; SILICON DIOXIDE; PHENOXYETHANOL; .ALPHA.-TOCOPHEROL ACETATE; WATER; NIACINAMIDE; CAPRYLYL TRISILOXANE; C13-15 ALKANE; ALKYL (C12-15) BENZOATE; DIMETHICONE/VINYL DIMETHICONE CROSSPOLYMER (SOFT PARTICLE); VINYLPYRROLIDONE/HEXADECENE COPOLYMER; XANTHAN GUM; INULIN; SOYBEAN LECITHIN; POTASSIUM CETYL PHOSPHATE; HYDROGENATED PALM GLYCERIDES; CETOSTEARYL ALCOHOL; CARBOMER COPOLYMER TYPE B (ALLYL PENTAERYTHRITOL CROSSLINKED); DIHEXADECYL PHOSPHATE; CETETH-10 PHOSPHATE; TRISODIUM ETHYLENEDIAMINE DISUCCINATE; EPIGALLOCATECHIN GALLATYL GLUCOSIDE

JAFRA BIOLAB Dark Spot Corrector Facial Cream Broad Spectrum SPF 30 Sunscreen

Active ingredient(s)

Avobenzone 3%
Homosalate 7%
Octisalate 5%
Octocrylene 10%

Purpose

Sunscreen

Uses

• helps prevent sunburn

• if used as directed with other sun protection measures (see Directions), decreases the risk of skin cancer and early skin aging

caused by the sun

Warnings

For external use only

Do not useon damaged or broken skin

When using this productkeep out of eyes. Rinse with water to remove.

Stop use and ask a doctor ifrash occurs

Keep out of reach of children. If swallowed, get medical help or contact a Poison Control Center right away.

Directions

• shake before use

• apply liberally and evenly 15 minutes before sun exposure

• reapply at least every 2 hours

• use a water resistant sunscreen if swimming or sweating

• children under 6 months of age: Ask a doctor

• Sun Protection Measures. Spending time in the sun increases your risk of skin cancer and early skin aging.

To decrease this risk, regularly use a sunscreen with a Broad Spectrum SPF value of 15 or higher and other sun protection measures including:
• limit time in the sun, especially from 10 a.m. – 2 p.m.
• wear long-sleeved shirts, pants, hats, and sunglasses

Other information

• protect this product from excessive heat and direct sun

Inactive ingredients

Water, Niacinamide, C12-15 Alkyl Benzoate, Styrene/Acrylates Copolymer, Potassium Cetyl Phosphate, Caprylyl Methicone, Silica, C13-15 Alkane, Hydrogenated Palm Glycerides, Cetearyl Alcohol, VP/Hexadecene Copolymer, Phenoxyethanol, Vinyl Dimethicone Crosspolymer, Acrylates/C10-30 Alkyl Acrylate Crosspolymer, Dicetyl Phosphate, Ceteth-10 Phosphate, Xanthan Gum, Trisodium Ethylenediamine Disuccinate, Tocopheryl Acetate, Ethylhexylglycerin, Inulin, Epigallocatechin Gallatyl Glucoside, Glycerin, Lecithin

Questions?
Call 1-800-551-2345 or visit www.jafra.com